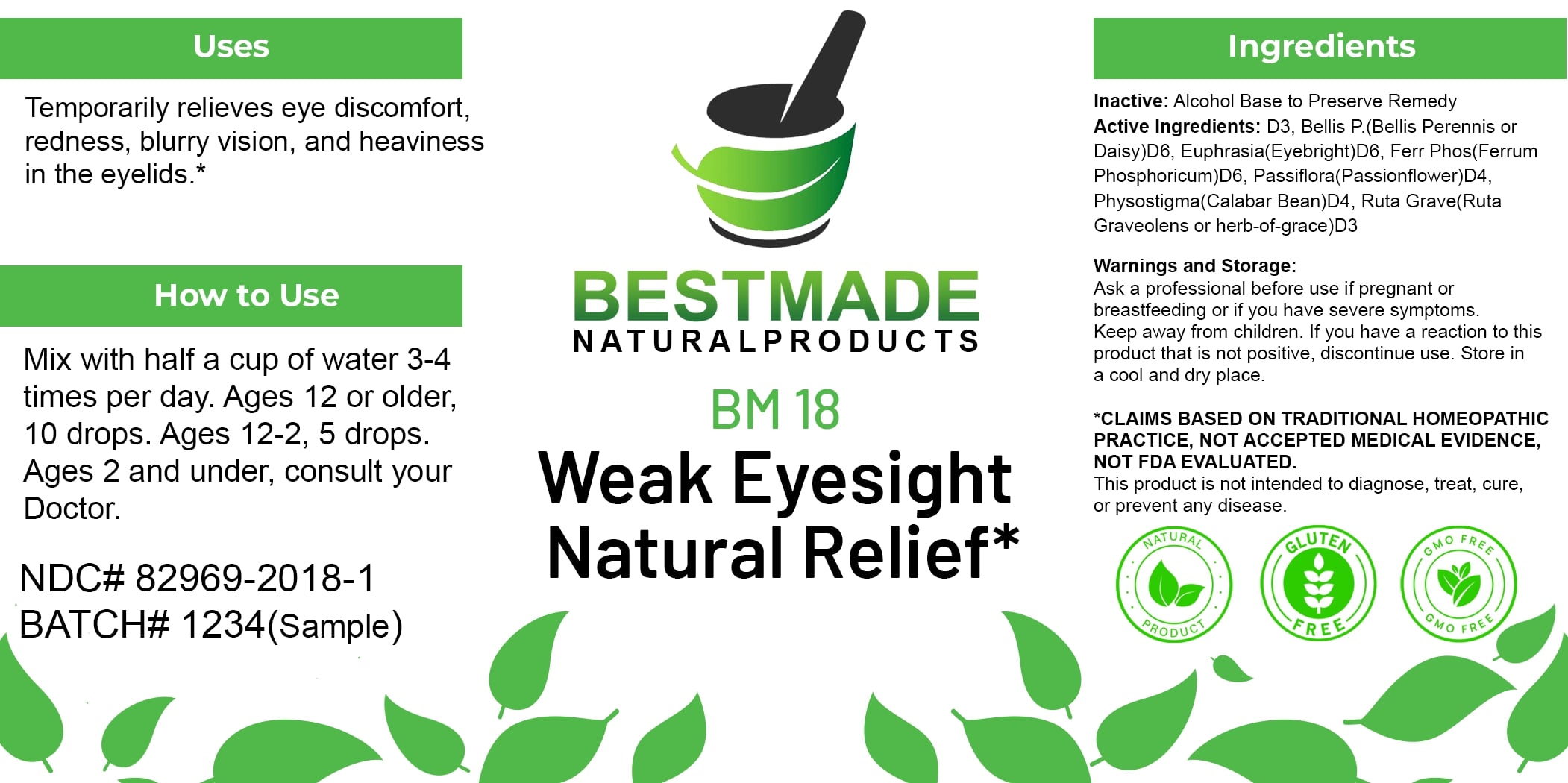 DRUG LABEL: Bestmade Natural Products BM18
NDC: 82969-2018 | Form: LIQUID
Manufacturer: Bestmade Natural Products
Category: homeopathic | Type: HUMAN OTC DRUG LABEL
Date: 20250122

ACTIVE INGREDIENTS: RUTA GRAVEOLENS FLOWERING TOP 30 [hp_C]/30 [hp_C]; ATROPA BELLADONNA 30 [hp_C]/30 [hp_C]; PASSIFLORA INCARNATA FLOWERING TOP 30 [hp_C]/30 [hp_C]; PHYSOSTIGMA VENENOSUM SEED 30 [hp_C]/30 [hp_C]; EUPHRASIA STRICTA 30 [hp_C]/30 [hp_C]; BELLIS PERENNIS 30 [hp_C]/30 [hp_C]; FERRIC PYROPHOSPHATE 30 [hp_C]/30 [hp_C]
INACTIVE INGREDIENTS: ALCOHOL 30 [hp_C]/30 [hp_C]

BM18

DOSAGE AND ADMINISTRATION

How to Use

Mix with half a cup of water 3-4 times per day. Ages 12 or older, 10 drops. Ages 12-2, 5 drops. Ages 2 and under, consult your Doctor.

INACTIVE INGREDIENT

Ingredients

Inactive: Alcohol Base to Preserve Remedy

Uses

Temporarily relieves eye discomfort, redness, blurry vision, and heaviness in the eyelids.*

*CLAIMS BASED ON TRADITIONAL HOMEOPATHIC PRACTICE, NOT ACCEPTED MEDICAL EVIDENCE. NOT FDA EVALUATED.

This product is not intended to diagnose, treat, cure, or prevent any disease.

ACTIVE INGREDIENT

Active Ingredients: D3, Bellis P. (Bellis Perennis or Daisy) D6, Euphrasia (Eyebright) D6, Ferr Phos (Ferrum Phosphoricum) D6, Passiflora (Passionflower) D4, Physostigma (Calabar Bean) D4, Ruta Grave (Ruta Graveolens or herb-of-grace) D3

KEEP OUT OF REACH OF CHILDREN

Warnings and Storage:

Ask a professional before use if pregnant or breastfeeding or if you have severe symptoms. Keep away from children. If you have a reaction to this product that is not positive, discontinue use. Store in a cool and dry place.

Uses

Temporarily relieves eye discomfort, redness, blurry vision, and heaviness in the eyelids.*

*CLAIMS BASED ON TRADITIONAL HOMEOPATHIC PRACTICE, NOT ACCEPTED MEDICAL EVIDENCE. NOT FDA EVALUATED.

This product is not intended to diagnose, treat, cure, or prevent any disease.

Warnings and Storage:

Ask a professional before use if pregnant or breastfeeding or if you have severe symptoms. Keep away from children. If you have a reaction to this product that is not positive, discontinue use. Store in a cool and dry place.

*CLAIMS BASED ON TRADITIONAL HOMEOPATHIC PRACTICE, NOT ACCEPTED MEDICAL EVIDENCE. NOT FDA EVALUATED.

This product is not intended to diagnose, treat, cure, or prevent any disease.

Entire package label